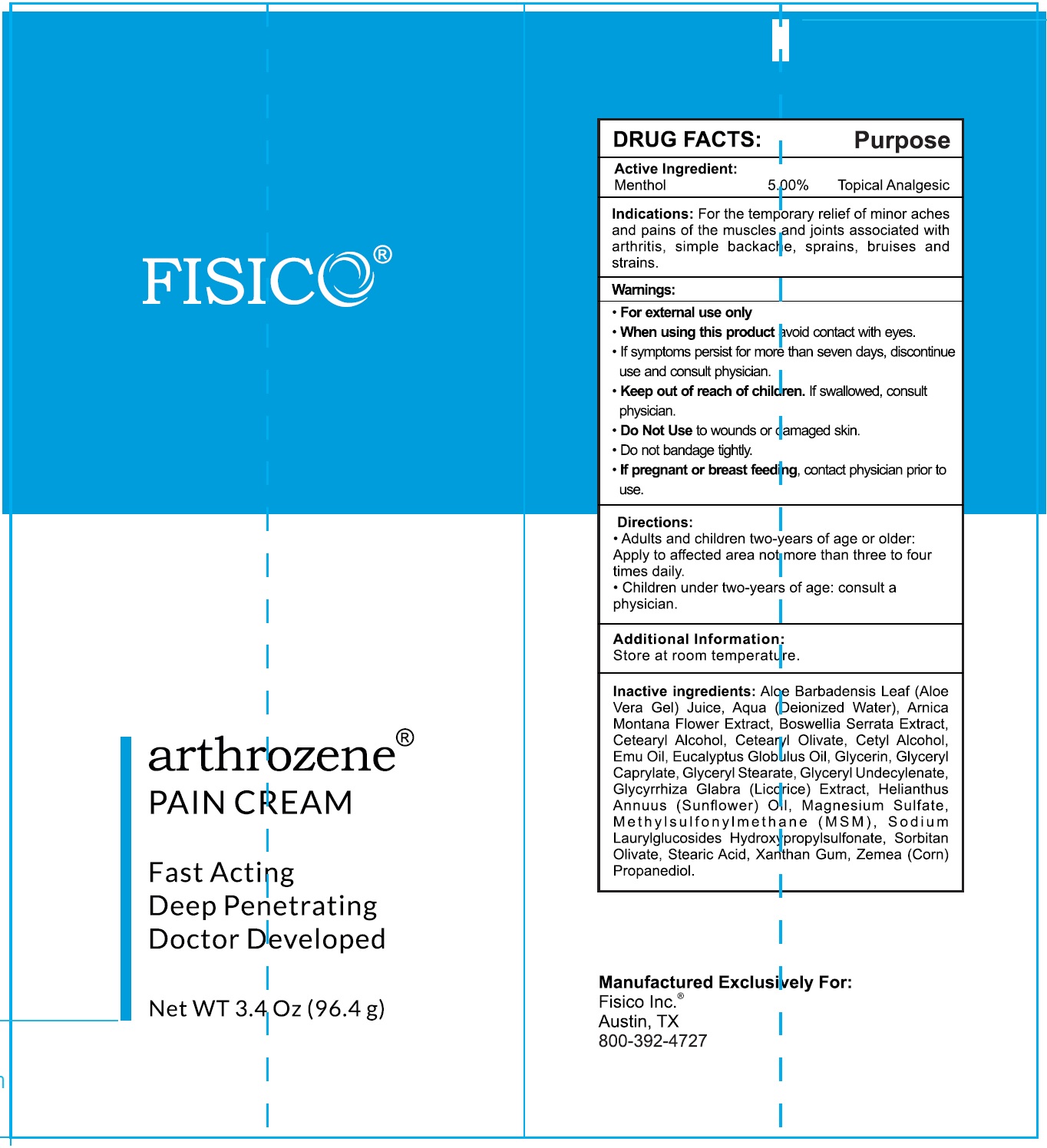 DRUG LABEL: FISICO Arthrozene Pain Cream
NDC: 83204-375 | Form: CREAM
Manufacturer: FISICO INC.
Category: otc | Type: HUMAN OTC DRUG LABEL
Date: 20231106

ACTIVE INGREDIENTS: MENTHOL 50 mg/1 g
INACTIVE INGREDIENTS: ALOE VERA LEAF; WATER; ARNICA MONTANA FLOWER; INDIAN FRANKINCENSE; CETOSTEARYL ALCOHOL; CETEARYL OLIVATE; CETYL ALCOHOL; EMU OIL; EUCALYPTUS OIL; GLYCERIN; GLYCERYL CAPRYLATE; GLYCERYL MONOSTEARATE; GLYCYRRHIZA GLABRA; HELIANTHUS ANNUUS FLOWERING TOP; MAGNESIUM SULFATE, UNSPECIFIED FORM; DIMETHYL SULFONE; SODIUM LAURYLGLUCOSIDES HYDROXYPROPYLSULFONATE; SORBITAN OLIVATE; STEARIC ACID; XANTHAN GUM; CORN

FISICO Arthrozene Pain Cream

Active Ingredient:

Menthol 5.00%

Purpose

Topical Analgesic

Indications:

For the temporary relief if minor aches and pains of the muscles and joints associated with arthritis, simple backache, sprains, bruises and strains.

Warnings:

- For external use only

When using this product

- avoid contact with eyes.
- If symptoms persist for more than seven days, discontinue use and consult physician.

Keep out of reach of children.

- If swallowed, consult physician.

Do Not Use

- to wounds or damaged skin.
- Do not bandage tightly.

If pregnant or breast feeding,

- contact physician prior to use.

Directions:

- Adults and children two-years of age or older: Apply to affected area not more than three to four times daily.
- Children under two-years of age: consult a physician.

Additional Information:

Store at room temperature.

Inactive ingredients:

Aloe Barbadensis Leaf (Aloe Vera Gel) Juice, Aqua (Deionized Water), Arnica Montana Flower Extract, Boswellia Serrata Extract, Cetearyl Alcohol, Cetearyl Olivate, Cetyl Alcohol, Emu Oil, Eucalyptus Globulus Oil, Glycerin, Glyceryl Caprylate, Glyceryl Stearate, Glyceryl Undecylenate, Glycyrrhiza Glabra (Licorice) Extract, Helianthus Annuus (Sunflower) Oil, Magnesium Sulfate, Methylsulfonylmethane (MSM), Sodium Laurylglucosides Hydroxypropylsulfonate, Sorbitan Olivate, Stearic Acid, Xanthan Gum, Zemea (Corn) Propanediol.